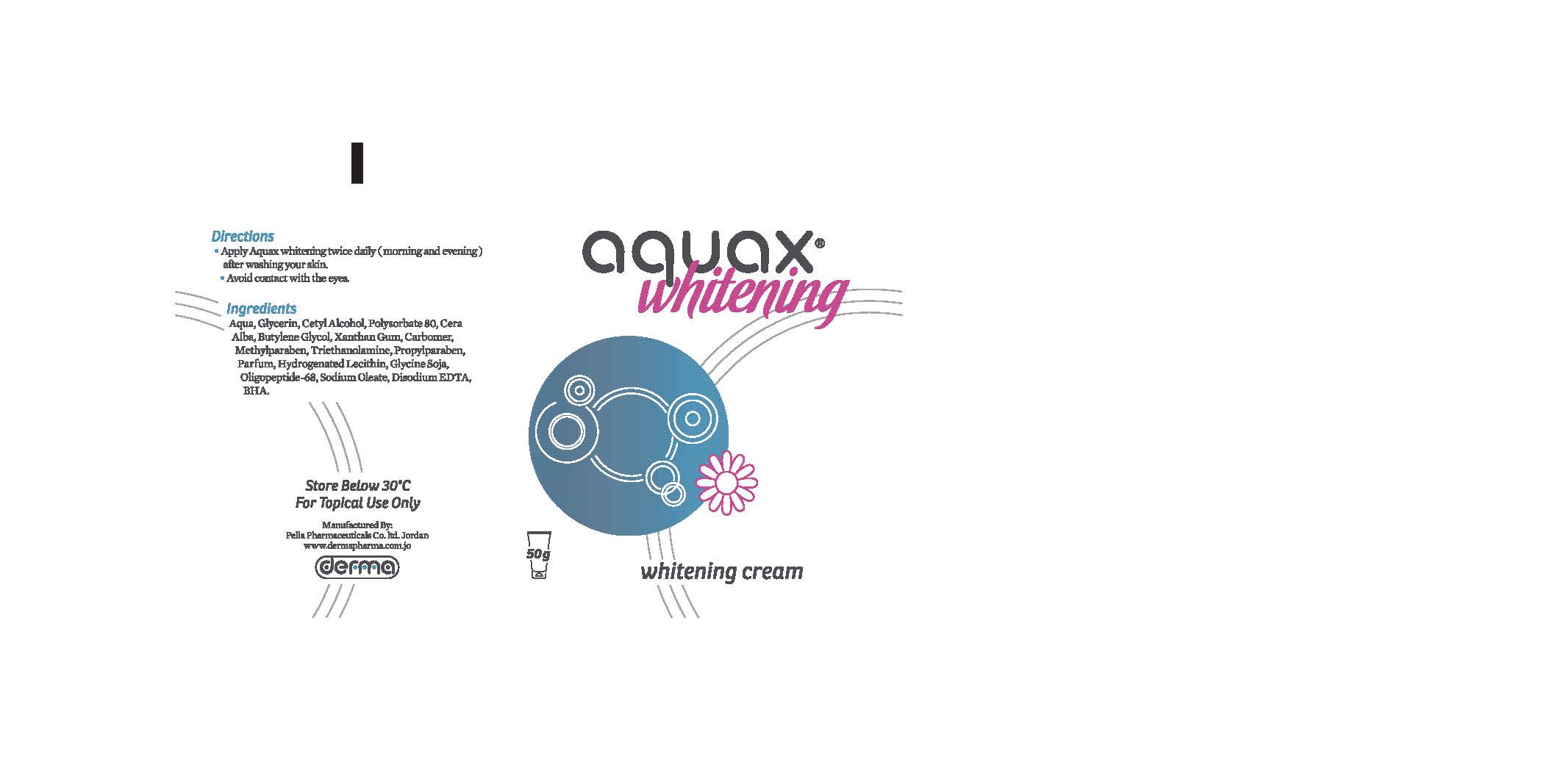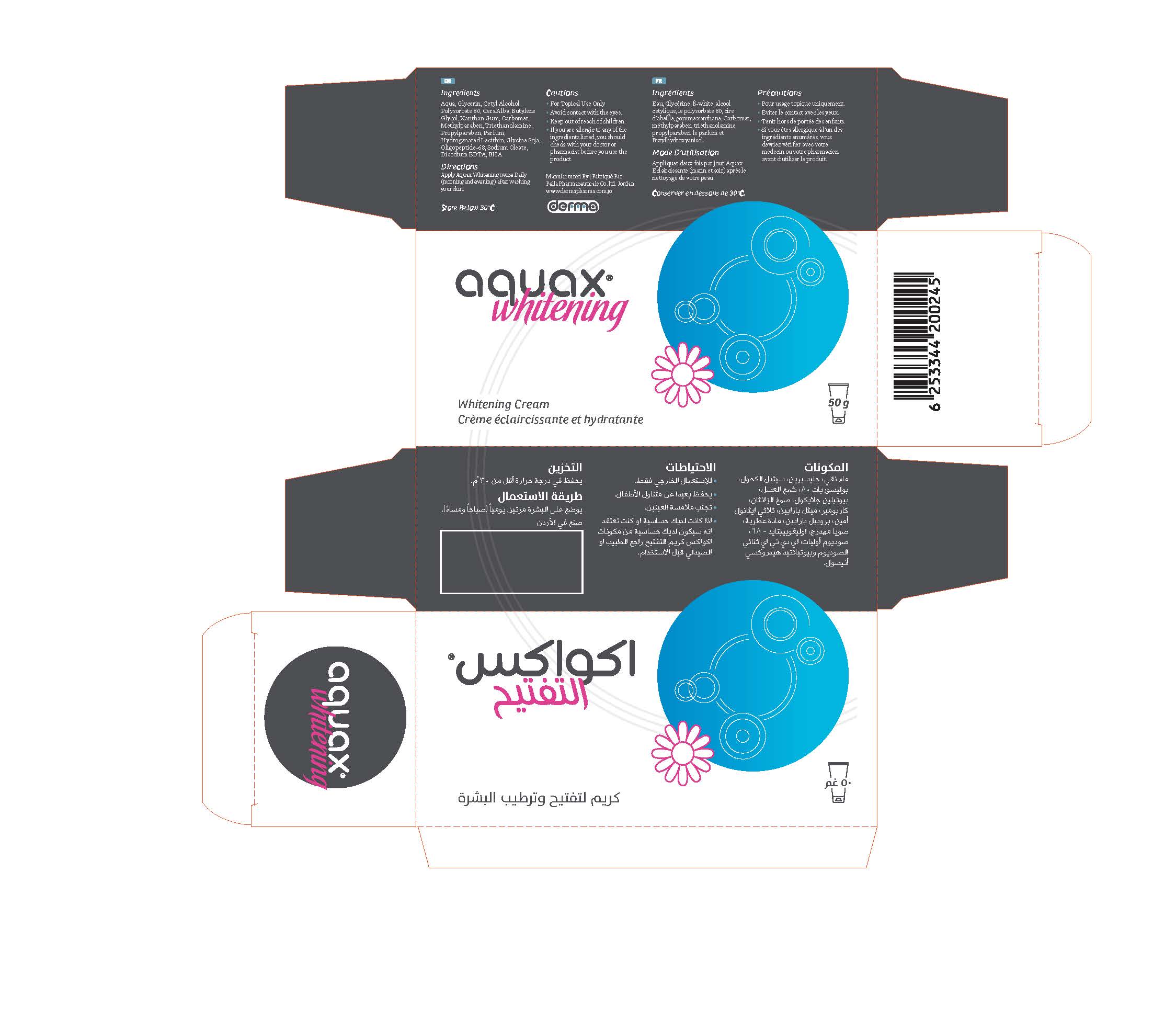 DRUG LABEL: Aquax Whitening
NDC: 82160-245 | Form: CREAM
Manufacturer: Pella Pharmaceuticals Co. Ltd
Category: otc | Type: HUMAN OTC DRUG LABEL
Date: 20211202

ACTIVE INGREDIENTS: AMINO ACIDS 0.2 mg/50 g
INACTIVE INGREDIENTS: SOYBEAN OIL; WHITE WAX; CARBOMER 940; PROPYLPARABEN; TROLAMINE; SODIUM OLEATE; GLYCERIN; BUTYLENE GLYCOL; HYDROGENATED SOYBEAN LECITHIN; POLYSORBATE 80; METHYLPARABEN; WATER; EDETATE DISODIUM ANHYDROUS; XANTHAN GUM; BUTYLATED HYDROXYANISOLE; CETYL ALCOHOL

Whitening

Forms and presentation

Cream: Tube of 50 g.

Active Ingredient

Oligopeptide-68

Inactive Ingredients

Aqua, Glycerin, Celyl Alcohol, Polysorbate 80, Cera Alba, Butylene Glycol, Xanthan Gum, Carbomer, Methylparaben, Triethanolamine, Propylparaben, Parfum, Hydrogenated Lecithin, Glycine Soja, Sodium Oleat, Disodium EDTA and BHA.

Purpose

Whitening

Properties

Aquax® Whitening is a cream that moisturizes, nourishes and lightens skin.

Indications

- Whitening of skin.
- Reduction of spots due to sunlight exposure.
- Pregnancy Mask (Melasma).
- Reduction of secular pigmentations of acne.
- Can be used on sensitive areas (armpits, genital region, knees, elbows .. etc.)
- The Product is Safe and Effective.

Precautions

Keep out of reach of children

Warnings

- For external use only
- Avoid contact with the eyes
- If you are allergic to any of the ingredients listed, you should check with your doctor or pharmacist before you use the product.

Contraindications

Hypersensitivity to any of the components.

Side effects

Aquax® Whitening Cream has no known side effect, because using it is safe.

Dosage and administration

Apply Aquax® Whitening Cream twice daily (morning and evening) on a cleaned skin.

Storage conditions

Store at a temperature below 30 ° C.